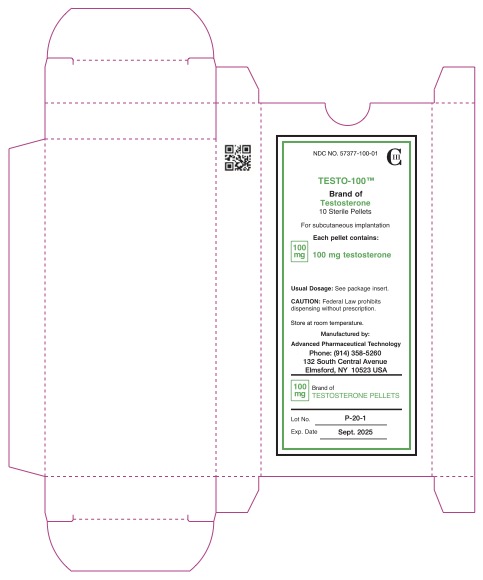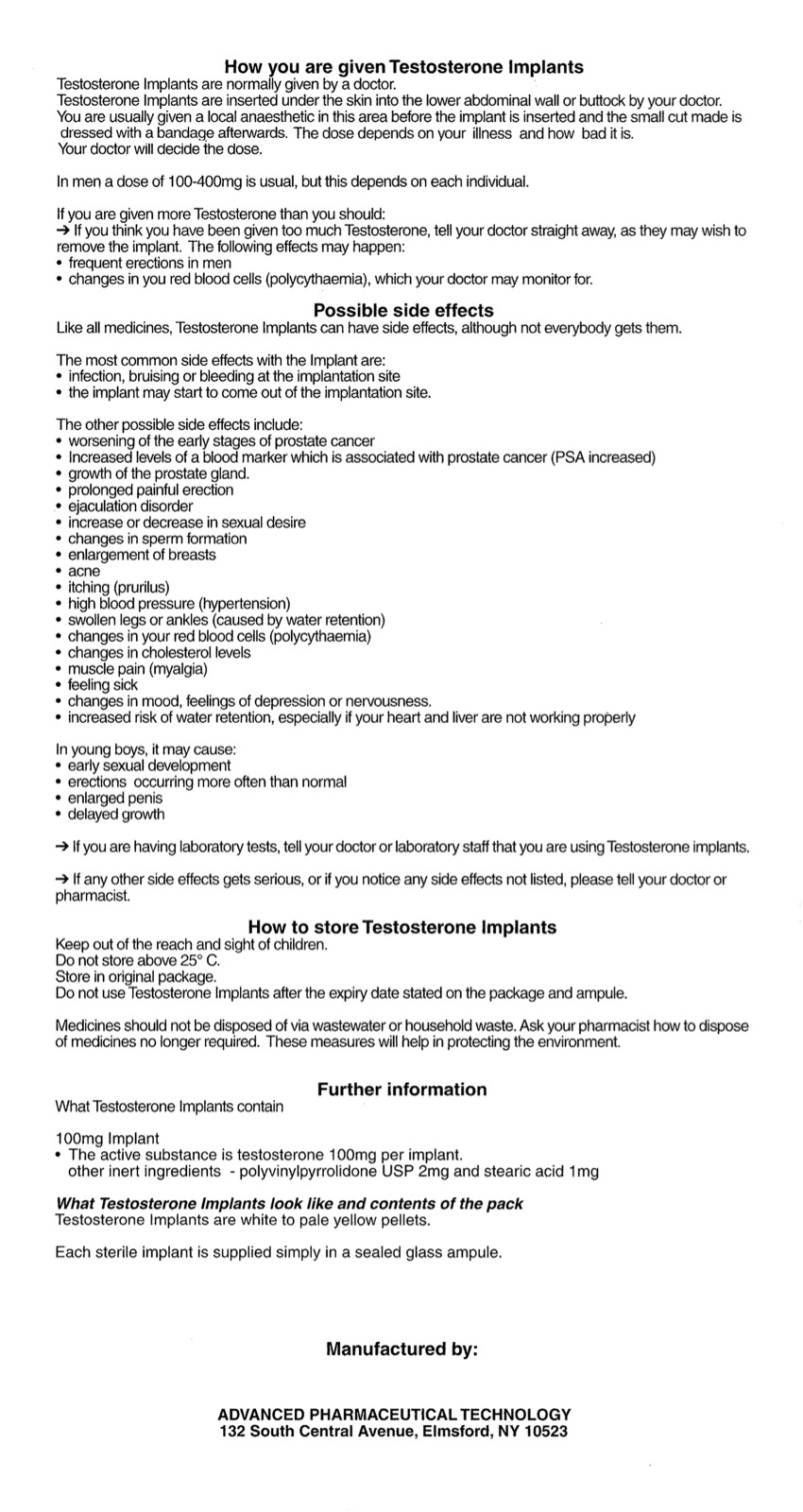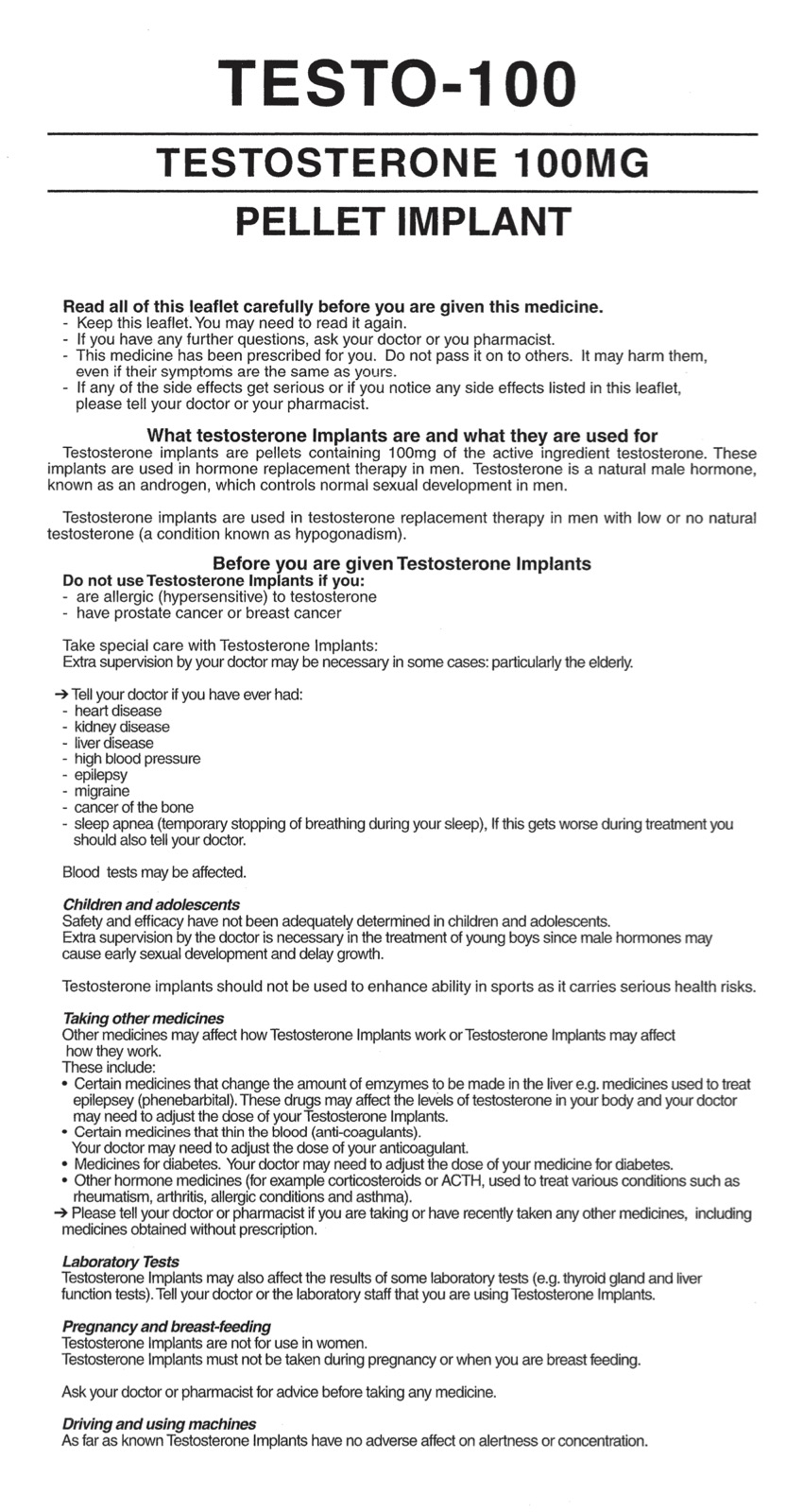 DRUG LABEL: Testo-100
NDC: 57377-100 | Form: PELLET, IMPLANTABLE
Manufacturer: Advanced Pharmaceutical Technology, Inc.
Category: prescription | Type: HUMAN PRESCRIPTION DRUG LABEL
Date: 20240905
DEA Schedule: CIII

ACTIVE INGREDIENTS: TESTOSTERONE 100 mg/1 1
INACTIVE INGREDIENTS: POVIDONE; STEARIC ACID

Testo-100

Read all of this leaflet carefully before you are given this medicine.

- Keep this leaflet. You may need to read it again.

- If you have any further questions, ask your doctor or your pharmacist.

- This medicine has been prescribed for you. Do not pass it on to others. It may harm them, even if their symptoms are the same as yours.

- If any of the side effects get serious or you notice any side effects listed in this leaflet, please tell your doctor or your pharmacist.

What testosterone Implants are and what they are used for

Testosterone implants are pellets containing 100mg of the active ingredient testosterone. These implants are used in hormone replacement therapy in men. Testosterone is a natural male hormone, known as an androgen, which controls normal sexual development in men.

Testosterone implants are used in testosterone replacement therapy in men with low or no natural testosterone (a condition known as hypogonadism).

Before you are given Testosterone Implants

Do not use Testosterone Implants if you:

- are allergic (hypersensitive) to testosterone

- have prostate cancer or breast cancer

Take special care with Testosterone Implants:

Extra supervision by your doctor may be necessary in some cases: particularly the elderly.

-> Tell your doctor if you have ever had:

- heart disease

- kidney disease

- liver disease

- high blood pressure

- epilepsy

- migraine

- cancer of the bone

- sleep apnea (temporary stopping of breathing during your sleep), If this gets worse during treatment you should also tell your doctor.

Blood tests may be affected.

Children and adolescents

Safety and efficacy have not been adequately determined in children and adolescents.

Extra supervision by the doctor is necessary in the treatment of young boys since male hormones may cause early sexual development and delay growth.

Testosterone implants should not be used to enhance ability in sports as it carries serious health risks.

Taking other medicines

Other medicines may affect how Testosterone Implants work or Testosterone Implants may affect how they work.

These include:

- Certain medicines that change the amount of enzymes to be made in the liver e.g. medicines used to treat epilepsy (phenobarbital). These drugs may affect the levels of testosterone in your body and your doctor may need to adjust the dose of your Testosterone Implants.
- Certain medicines that thin the blood (anti-coagulants).

Your doctor may need to adjust the dose of your anticoagulant.

- Medicines for diabetes. Your doctor may need to adjust the dose of your medicine for diabetes.
- Other hormone medicines (for example corticosteroids or ACTH, used to treat various conditions such as rheumatism, arthritis, allergic conditions and asthma).

-> Please tell your doctor or pharmacist if you are taking or have recently taken any other medicines, including medicines obtained without prescription.

Laboratory Tests

Testosterone Implants may also affect the results of some laboratory tests (e.g. thyroid gland and liver function tests). Tell your doctor or the laboratory staff that you are using Testosterone Implants.

Pregnancy and breast-feeding

Testosterone Implants are not for use in women.

Testosterone Implants must not be taken during pregnancy or when you are breast feeding.

Ask your doctor or pharmacist for advice before taking any medicine.

Driving and using machines

As far as known Testosterone Implants have no adverse affects on alertness or concentration.

How you are given Testosterone Implants

Testosterone Implants are normally given by a doctor.

Testosterone Implants are inserted under the skin into the lower abdominal wall or buttock by your doctor.

You are usually given a local anaesthetic in this area before the implant is inserted and the small cut made is dressed with a bandage afterwards. The implant usually lasts for 4 or 5 months. the dose depends on your illness and how bad it is.

Your doctor will decide the dose.

In men a dose of 100-400mg is usual, but this depends on each individual.

If you are given more Testosterone than you should:

-> If you think you have been given too much Testosterone, tell your doctor straight away, as they may wish to remove the implant. The following effects may happen:

- frequent erections in men
- changes in your red blood cells (polycythemia), which your doctor may monitor for.

Possible side effects

Like all medicines, Testosterone Implants can have side effects, although not everybody gets them.

The most common side effect with the Implant are:

- infection, bruising or bleeding at the implantion site
- the implant may start to come out of the implantation site.

The other possible side effects include:

- worsening of the early stages of prostate cancer
- Increased levels of a blood marker which is associated with prostate cancer (PSA increased)
- growth of the prostate gland
- prolonged painful erection
- ejaculation disorder
- increase or decrease in sexual desire
- changes in sperm formation
- enlargement of breasts
- acne
- itching (pruritus)
- high blood pressure (hypertension)
- swollen legs or ankles (caused by water retention)
- changes in your red blood cells (polycythemia)
- changes in cholesterol levels
- muscle pain (myalgia)
- feeling sick
- changes in mood, feelings of depression or nervousness.
- increased risk of water retention, especially if your heart and liver are not working properly

In young boys, it may cause:

- early sexual development
- erections occurring more often than normal
- enlarged penis
- delayed growth

-> If you are having laboratory tests, tell your doctor or laboratory staff that you are using Testosterone Implants.

-> If any other side effects get serious, or if you notice any side effects not listed, please tell your doctor or pharmacist.

How to store Testosterone Implants

Keep out of reach of children.

Do not store above 25oC.

Store in original package.

Do not use Testosterone Implants after the expiry date stated on the package and ampule.

Medicines should not be disposed of via wastewater or houdehold waste. Ask your pharmacist how to dispose of medicines no longer required. These measures will help in protecting the enviroment.

Further Information

What Testosterone Implants contain

100mg Implant

- The active substance is testosterone 100mg per implant.

other inert ingredients - polyvinylpyrrolidone USP 2mg and stearic acid 1mg

What Testosterone Implants look like and contents of the pack

Testosterone Implants are white to pale yellow pellets.

Each sterile implant is supplied simply in a sealed glass ampule.

Manufactured by:

ADVANCED PHARMACEUTICAL TECHNOLOGY

132 South Central Avenue

Elmsford, NY 10523

Testo-100 (57377-100-01)

Testo-100

Brand of

Testosterone

HOW SUPPLIED

10 Sterile Pellets

DOSAGE FORMS AND STRENGTHS

For subcutaneous implantation

Each pellet contains:

100mg testosterone

Usual Dosage:See package insert.

Caution:

Federal Law prohibits dispensing without presciption.

STORAGE AND HANDLING

Store at room temperature.